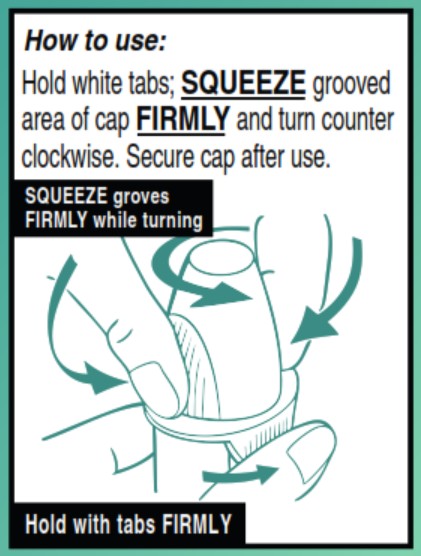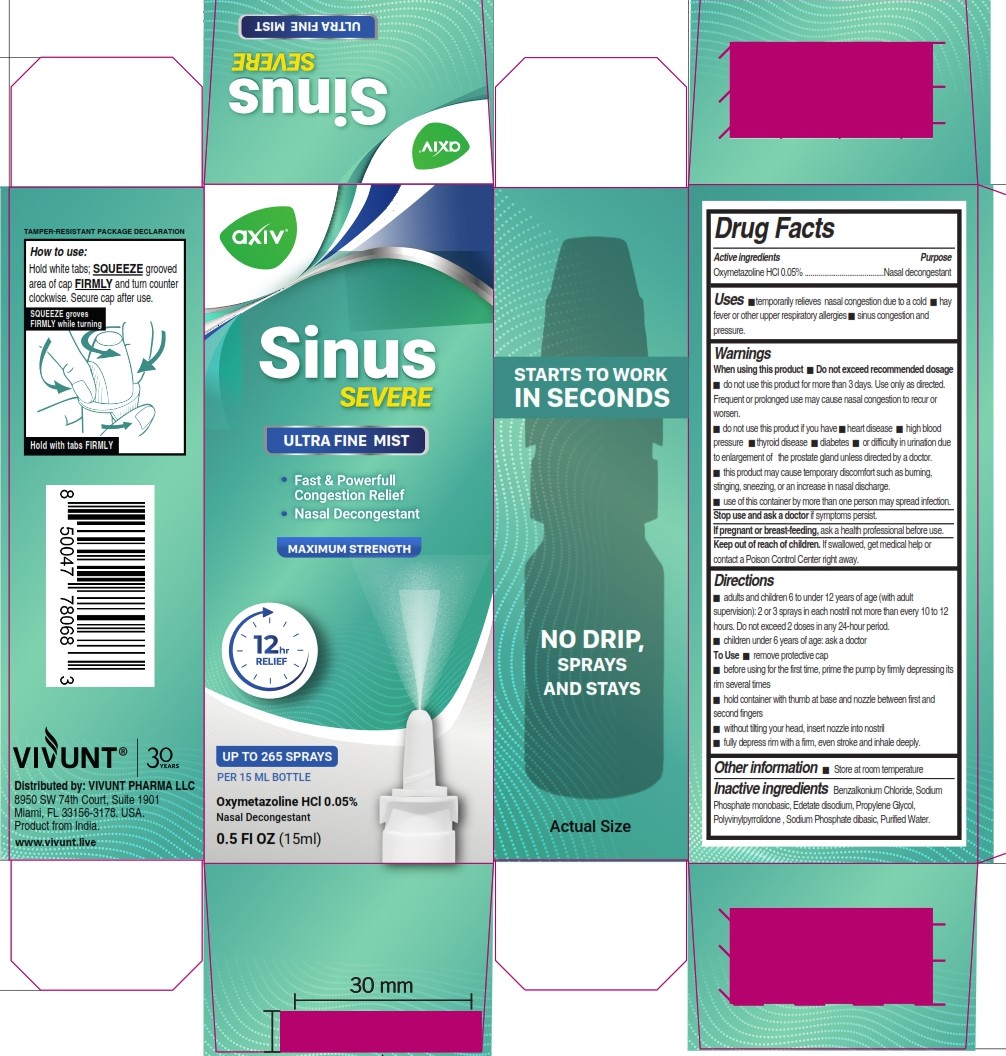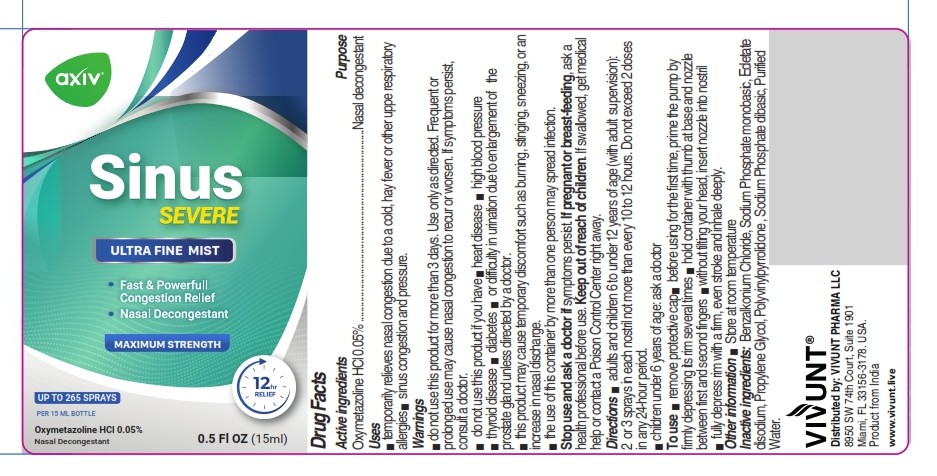 DRUG LABEL: AXIV Sinus Severe Ultra Fine Mist
NDC: 82706-030 | Form: AEROSOL, SPRAY
Manufacturer: VIVUNT PHARMA LLC
Category: otc | Type: HUMAN OTC DRUG LABEL
Date: 20260223

ACTIVE INGREDIENTS: OXYMETAZOLINE HYDROCHLORIDE 0.5 mg/1 mL
INACTIVE INGREDIENTS: SODIUM PHOSPHATE, DIBASIC, ANHYDROUS; SODIUM PHOSPHATE, MONOBASIC, ANHYDROUS; POVIDONE K30; EDETATE DISODIUM; PROPYLENE GLYCOL; WATER; BENZALKONIUM CHLORIDE

AXIV Sinus Severe Nasal Spray

Drug Facts

Active ingredients

- Oxymetazoline HCl 0.05%

Purpose

- Nasal decongestant

Uses

- temporarily relieves nasal congestion due to a cold
- hay fever or other upper respiratory allergies
- sinus congestion and pressure.

Warnings

When using this product

- Do not exceed recommended dosage
- do not use this product for more than 3 days. Use only as directed. Frequent or prolonged use may cause nasal congestion to recur or worsen.
- do not use this product if you have
- heart disease
- high blood pressure
- thyroid disease
- diabetes
- or difficulty in urination due to enlargement of the prostate gland unless directed by a doctor.
- this product may cause temporary discomfort such as burning, stinging, sneezing, or an increase in nasal discharge.
- use of this comtainer by more than one person may spread infection.

Stop use and ask a doctor

if symptoms persist.

If pregnant or breast-feeding,

ask a health professional before use.

Keep out of reach of children.

OVERDOSAGE

If swallowed, get medical help or contact a Poison Control Center right away.

Directions

- adults and children 6 to under 12 years of age (with adult supervision): 2 or 3 sprays in each nostril not more than every 10 to 12 hours. Do not exceed 2 doses in any 24-hour period.
- children under 6 years of age: ask a doctor

To Use

- remove protective cap
- before using for the first time, prime the pump by firmly depressing its rim several times
- hold container with thumb at base and nozzle between first and second fingers
- without tilting your head, inset nozzle into nostril
- fully depress rim with a firm, even stroke and inhale deeply.

How to use:

Hold white tabs; SQUEEZE grooved area of cap FIRMLY and turn counter clockwise. Secure cap after use.

Other information

- Store at room temperature

Inactive ingredients

Benzalkonium Chloride, Sodium Phosphate monobasic, Edetate disodium, Propylene Glycol, Polyvinylpyrrolidone, Sodium Phosphate dibasic, Purified Water.

Distributed by: VIVUNT PHARMA LLC

8950 SW 74th Court, Suite 1901

Miami, FL 33156-3178. USA.

Product from India.

www.vivunt.live

PACKAGE LABEL

axiv®

Sinus SEVERE

ULTRA FINE MIST

- Fast & Powerfull Congestion Relief
- Nasal Decongestant

MAXIMUM STRENGTH

UP TO 265 SPRAYS

PER 15 ML BOTTLE

Oxymetazoline HCl 0.05%

Nasal Decongestant

0.5 Fl OZ (15ml)

axiv®

Sinus SEVERE

ULTRA FINE MIST

- Fast & Powerfull Congestion Relief
- Nasal Decongestant

MAXIMUM STRENGTH

UP TO 265 SPRAYS

PER 15 ML BOTTLE

Oxymetazoline HCl 0.05%

Nasal Decongestant

0.5 Fl OZ (15 ml)